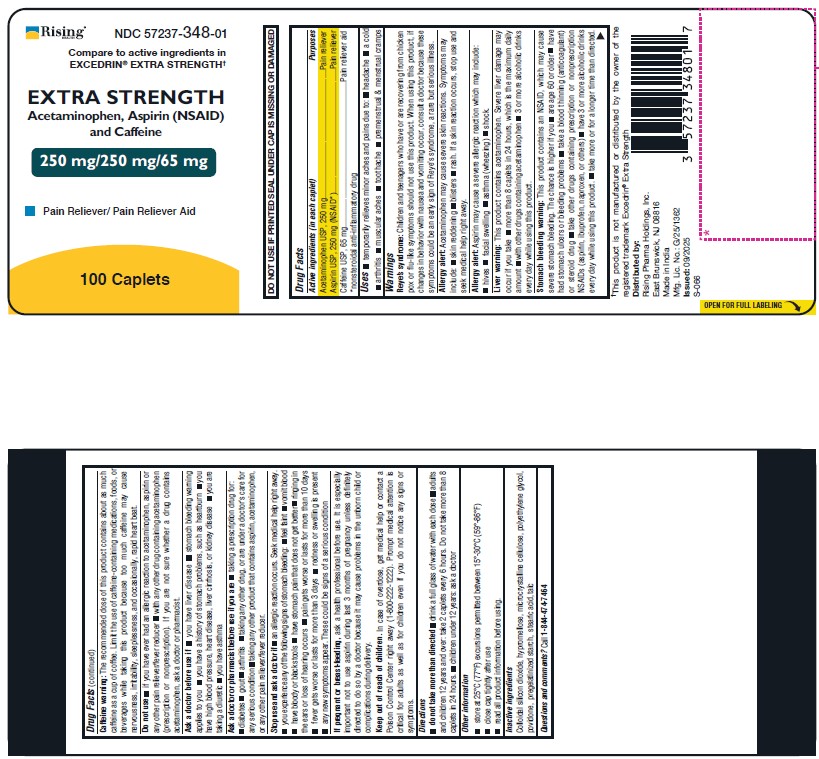 DRUG LABEL: Acetaminophen, Aspirin and Caffeine
NDC: 57237-348 | Form: TABLET
Manufacturer: Rising Pharma Holdings, Inc.
Category: otc | Type: HUMAN OTC DRUG LABEL
Date: 20251006

ACTIVE INGREDIENTS: ACETAMINOPHEN 250 mg/1 1; ASPIRIN 250 mg/1 1; CAFFEINE 65 mg/1 1
INACTIVE INGREDIENTS: SILICON DIOXIDE; HYPROMELLOSE, UNSPECIFIED; MICROCRYSTALLINE CELLULOSE; POLYETHYLENE GLYCOL, UNSPECIFIED; POVIDONE; STARCH, CORN; SODIUM STARCH GLYCOLATE TYPE A; STEARIC ACID; TALC

Compare to active ingredients in EXCEDRIN® EXTRA STRENGTH^+
EXTRA STRENGTH
Acetaminophen, Aspirin (NSAID) and Caffeine
250 mg/250 mg/65 mg
Pain Reliever/ Pain Reliever Aid
100 Caplets

DO NOT USE IF PRINTED SEAL UNDER CAP IS MISSING OR DAMAGED Drug Facts

Active ingredients (in each caplet) Purposes
Acetaminophen USP, 250 mg...............................................................Pain reliever
Aspirin USP, 250 mg (NSAID*).............................................................Pain reliever
Caffeine USP, 65 mg........................................................................Pain reliever aid
*nonsteroidal anti-inflammatory drug

Uses

- temporarily relieves minor aches and pains due to:
- headache
- a cold
- arthritis
- muscular aches
- toothache
- premenstrual & menstrual cramps

Warnings

Reye’s syndrome: Children and teenagers who have or are recovering from chicken pox or flu-like symptoms should not use this product. When using this product, if changes in behavior with nausea and vomiting occur, consult a doctor because these symptoms could be an early sign of Reye’s syndrome, a rare but serious illness.

Allergy alert: Acetaminophen may cause severe skin reactions. Symptoms may include:

- skin reddening
- blisters
- rash. If a skin reaction occurs, stop use and seek medical help right away.

Allergy alert: Aspirin may cause a severe allergic reaction which may include:

- hives
- facial swelling
- asthma (wheezing)
- shock.

Liver warning: This product contains acetaminophen. Severe liver damage may occur if you take

- more than 8 caplets in 24 hours, which is the maximum daily amount
- with other drugs containing acetaminophen
- 3 or more alcoholic drinks every day while using this product.

Stomach bleeding warning: This product contains an NSAID, which may cause severe stomach bleeding. The chance is higher if you

- are age 60 or older
- have had stomach ulcers or bleeding problems
- take a blood thinning (anticoagulant) or steroid drug
- take other drugs containing prescription or nonprescription NSAIDs (aspirin, ibuprofen, naproxen, or others)
- have 3 or more alcoholic drinks every day while using this product.
- take more or for a longer time than directed.

Caffeine warning: The recommended dose of this product contains about as much caffeine as a cup of coffee. Limit the use of caffeine-containing medications, foods, or beverages while taking this product because too much caffeine may cause nervousness, irritability, sleeplessness, and occasionally, rapid heart beat.

Do not use

- if you have ever had an allergic reaction to acetaminophen, aspirin or any other pain reliever/fever reducer
- with any other drug containing acetaminophen (prescription or nonprescription). If you are not sure whether a drug contains acetaminophen, ask a doctor or pharmacist.

Ask a doctor before use if

- you have liver disease
- stomach bleeding warning applies to you
- you have a history of stomach problems, such as heartburn
- you have high blood pressure, heart disease, liver cirrhosis, or kidney disease
- you are taking a diuretic
- you have asthma

Ask a doctor or pharmacist before use if you are

- taking a prescription drug for:
- diabetes
- gout
- arthritis
- taking any other drug, or are under a doctor's care for any serious condition
- taking any other product that contains aspirin, acetaminophen, or any other pain reliever/fever reducer.

Stop use and ask a doctor if

- an allergic reaction occurs. Seek medical help right away.
- you experience any of the following signs of stomach bleeding:
- feel faint
- vomit blood
- have bloody or black stools
- have stomach pain that does not get better
- ringing in the ears or loss of hearing occurs
- pain gets worse or lasts for more than 10 days
- fever gets worse or lasts for more than 3 days
- redness or swelling is present
- any new symptoms occur. These could be signs of a serious condition

PREGNANCY OR BREAST FEEDING

If pregnant or breast-feeding, ask a health professional before use. It is especially important not to use aspirin during last 3 months of pregnancy unless definitely directed to do so by a doctor because it may cause problems in the unborn child or complications during delivery.

Keep out of reach of children.

In case of overdose, get medical help or contact a Poison Control Center right away (1-800-222-1222). Prompt medical attention is critical for adults as well as for children even if you do not notice any signs or symptoms.

Directions

- do not take more than directed
- drink a full glass of water with each dose
- adults and children 12 years and over: take 2 caplets every 6 hours. Do not take more than 8 caplets in 24 hours.
- children under 12 years: ask a doctor

Other information

- store at 25°C (77°F) excursions permitted between 15°-30°C (59°-86°F)
- close cap tightly after use
- read all product information before using.

Inactive ingredients

Colloidal silicon dioxide , hypromellose, microcrystalline cellulose , polyethylene glycol, povidone, pregelatinized starch, stearic acid, talc

Questions and comments? Call 1-844-474-7464

Distributed by:
Rising Pharma Holdings, Inc.
East Brunswick, NJ 08816 Made in India Mfg. Lic. No.: G/25/1362

Issued: 09/2025
S-066

^+This product is not manufactured or distributed by the owner of the registered trademark Excedrin® Extra Strength

PACKAGE LABEL.PRINCIPAL DISPLAY PANEL

EXTRA STRENGTH Acetaminophen, Aspirin (NSAID) and Caffeine
250mg/250mg/65mg

NDC 57237-348-01

100 Caplets